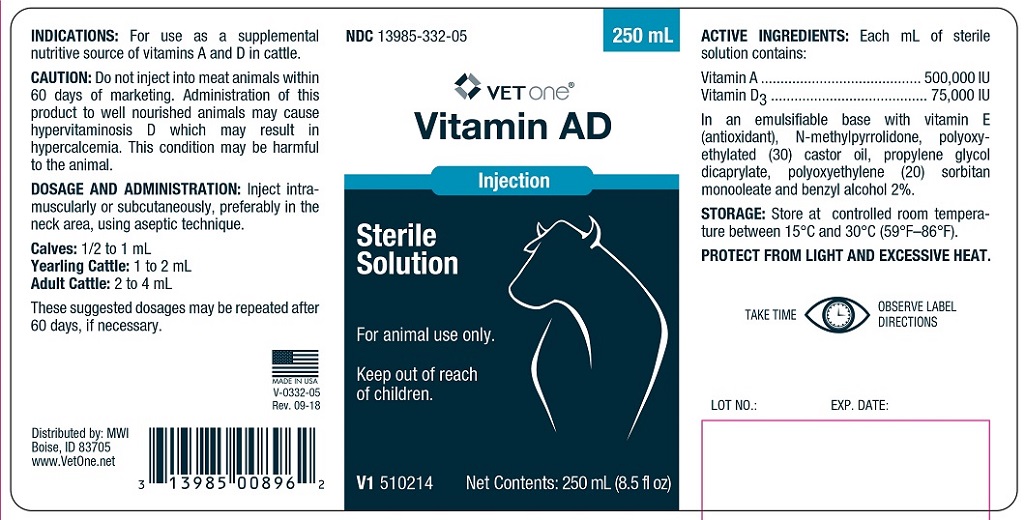 DRUG LABEL: Vitamin AD
NDC: 13985-332 | Form: INJECTION
Manufacturer: MWI Veterinary Supply, Inc.
Category: animal | Type: OTC ANIMAL DRUG LABEL
Date: 20190418

ACTIVE INGREDIENTS: RETINOL 500000 [iU]/1 mL; CHOLECALCIFEROL 75000 [iU]/1 mL

VITAMIN AD INJECTION

INDICATIONS AND USAGE

Sterile Solution

For Animal Use Only
Keep Out of Reach of Children

INDICATIONS

For use as a supplemental nutritive source of vitamins A and D in cattle.

CAUTION

Do not inject into meat animals within 60 days of marketing.

Administration of this product to well nourished animals may cause hypervitaminosis D which may result in hypercalcemia. This condition may be harmful to the animal.

DOSAGE AND ADMINISTRATION

Inject intramuscularly or subcutaneously preferably in the neck area using aseptic technique.

Calves- 1/2 to 1 mL,
Yearling Cattle- 1 to 2 mL
Adult Cattle- 2 to 4 mL

These suggested dosage may be repeated after 60 days, if necessary.

COMPONENTS

Each mL of sterile solution contains:

ACTIVE INGREDIENTS

Vitamin A . . . . . . . . . 500,000 IU
Vitamin D3 . . . . . . . . . 75,000 IU

INACTIVE INGREDIENTS

In an emulsifiable base with vitamin E (antioxidant), N-methylpyrrolidone, polyoxyethylated (30) castor oil, propylene glycol dicaprylate, polyoxyethylene (20) sorbitan monooleate and benzyl alcohol 2%.

STORAGE

Store at controlled room temperature between 15o and 30oC (59-86oF).

PROTECT FROM LIGHT AND EXCESSIVE HEAT.

TAKE TIME OBSERVE LABEL DIRECTIONS